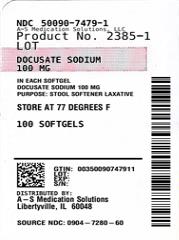 DRUG LABEL: DOCUSATE SODIUM
NDC: 50090-7479 | Form: CAPSULE, LIQUID FILLED
Manufacturer: A-S Medication Solutions
Category: otc | Type: HUMAN OTC DRUG LABEL
Date: 20241230

ACTIVE INGREDIENTS: DOCUSATE SODIUM 100 mg/1 1
INACTIVE INGREDIENTS: RED 40; KI5; GELATIN; GLYCERIN; POLYETHYLENE GLYCOL, UNSPECIFIED; PROPYLENE GLYCOL; AQUA; SORBITOL; ANHYDROUS CITRIC ACID

Drug Facts

Active ingredient (in each softgel)

Docusate Sodium 100 mg

Purpose

Stool softener

Uses

- for temporary relief of occasional constipation and irregularity
- this product generally produces bowel movement in 12 to 72 hours

Warnings

Ask a doctor before use if you have

- stomach pain, nausea or vomitting
- a sudden change in bowel habits that lasts more than 2 weeks

Ask a doctor or pharmacist before use if you arepresently taking mineral oil

Stop use and ask a doctor if

- you have rectal bleeding or no bowel movement after using this product. These could be signs of a serious condition.
- you need to use a laxative for more than 1 week

PREGNANCY OR BREAST FEEDING

If pregnant or breast-feeding,ask a health professional before use.

Keep out of reach of children.In case of overdose, get medical help or contact a Poison Control Center right away.

Directions

take with a glass of water

Adults and children 12 years and over | 1 to 3 softgels daily. This dose may be taken as a single daily dose or in divided doses.
Children 2 to under 12 years of age | 1 softgel daily
children under 2 years of age | ask a doctor

Other information

- each softgel contains: sodium 5 mg
- store at room temperature 15°-30°C (59°-86°F)
- protect from excessive humidity

Inactive ingredients

FD&C Red # 40, FD&C Yellow #6, gelatin, glycerin, polyethylene glycol, propylene glycol, sorbitol special, citric acid, purified water and white edible ink

Manufactured by:
Humanwell PuraCap Pharmaceutical (Wuhan) Ltd.
Wuhan, Hubei
430206, China

HOW SUPPLIED

Product: 50090-7479

NDC: 50090-7479-1 100 CAPSULE, LIQUID FILLED in a BOTTLE, PLASTIC

NDC: 50090-7479-4 30 CAPSULE, LIQUID FILLED in a BOTTLE, PLASTIC